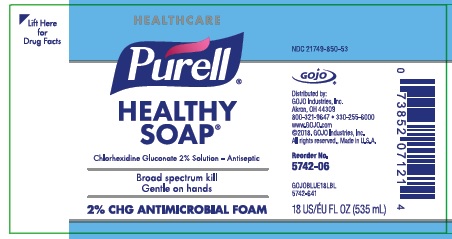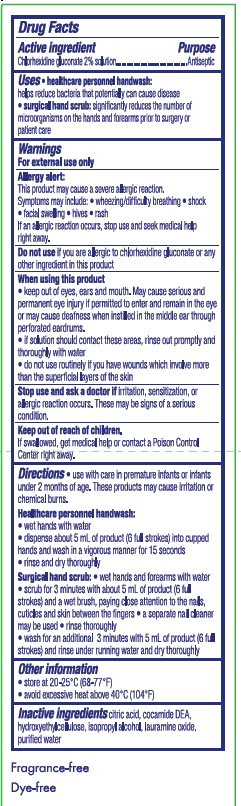 DRUG LABEL: Provon Antimicrobial Foam Handwash
NDC: 21749-850 | Form: SOLUTION
Manufacturer: Gojo Industries, Inc.
Category: otc | Type: HUMAN OTC DRUG LABEL
Date: 20221220

ACTIVE INGREDIENTS: CHLORHEXIDINE GLUCONATE 20 mg/1 mL
INACTIVE INGREDIENTS: CITRIC ACID MONOHYDRATE; COCO DIETHANOLAMIDE; HYDROXYETHYL CELLULOSE (2000 MPA.S AT 1%); ISOPROPYL ALCOHOL; LAURAMINE OXIDE; WATER

Drug Facts

Active ingredient

chlorhexidine gluconate 2% solution

Purpose

surgical hand scrub

healthcare personnel handwash

Uses

- surgical hand scrub: significantly reduces the number of microorganisms on the hands and forearms prior to surgery or patient care
- healthcare personnel handwash: helps reduce bacteria that potentially can cause disease

Warnings

For external use only

Do not use

- if you are allergic to chlorhexidine gluconate or any other ingredient in this product

Allergy alert:

This product may cause a serious allergic reaction. Symptoms may include:

- wheezing/difficulty breathing
- shock
- facial swelling
- hives
- rash

If an allergic reaction occurs, stop use and seek medical help right away.

When using this product

- keep out of eyes, ears, and mouth
- may cause serious and permanent eye injury if permitted to enter and remain in the eye or may cause deafness when instilled in the middle ear through perforated eardrums
- if solution should contact these areas, rinse out promptly and thoroughly with water
- Do not use routinely if you have wounds which involve more than the superficial layers of the skin

Stop use and ask a doctor if irritation, sensitization or allergic reaction occurs. These may be signs of a serious condition.

Keep out of reach of children. If swallowed, get medical help or contact a Poison Control Center right away.

Directions

- Use with care in premature infants or infants under 2 months of age. These products may cause irritation or chemical burns.

Surgical hand scrub:

- wet hands and forearms with water
- scrub for 3 minutes with 5 ml of solution and a wet brush paying close attention to the nails, cuticles, and interdigital space
- a separate nail cleaner may be used
- rinse thoroughly
- wash for an additional 3 minutes with 5 ml of solution and rinse under running water
- dry thoroughly

Healthcare personnel handwash:

- wet hands with water
- dispense 5 ml of solution (4 full strokes) into cupped hands, wash in a vigorous manner for 15 seconds, and rinse under running water
- dry thoroughly

Other information

- store at 20-25° C (68-77° F)
- avoid excessive heat above 40° C (104° F)

Inactive ingredients

citric add. cocamide DEA, hydroxyethylcellulose, isopropyl alcohol, lauramine oxide, purified water

Questions or comments?

call 1-800-321-9647 Monday through Friday 8 AM to 5 PM MST

PACKAGE LABEL

NDC 21749-850-53

Chlorhexidine Gluconate 2% Solution

Antiseptic Foam Handwash

Distributed by:

Gojo Industries, Inc.

Akron, OH 60085 USA

330-255-6000

www.gojo.com

GOJO18BTLLBL

Gojo® 2018

Net Wt 18 fl oz (535 mL)